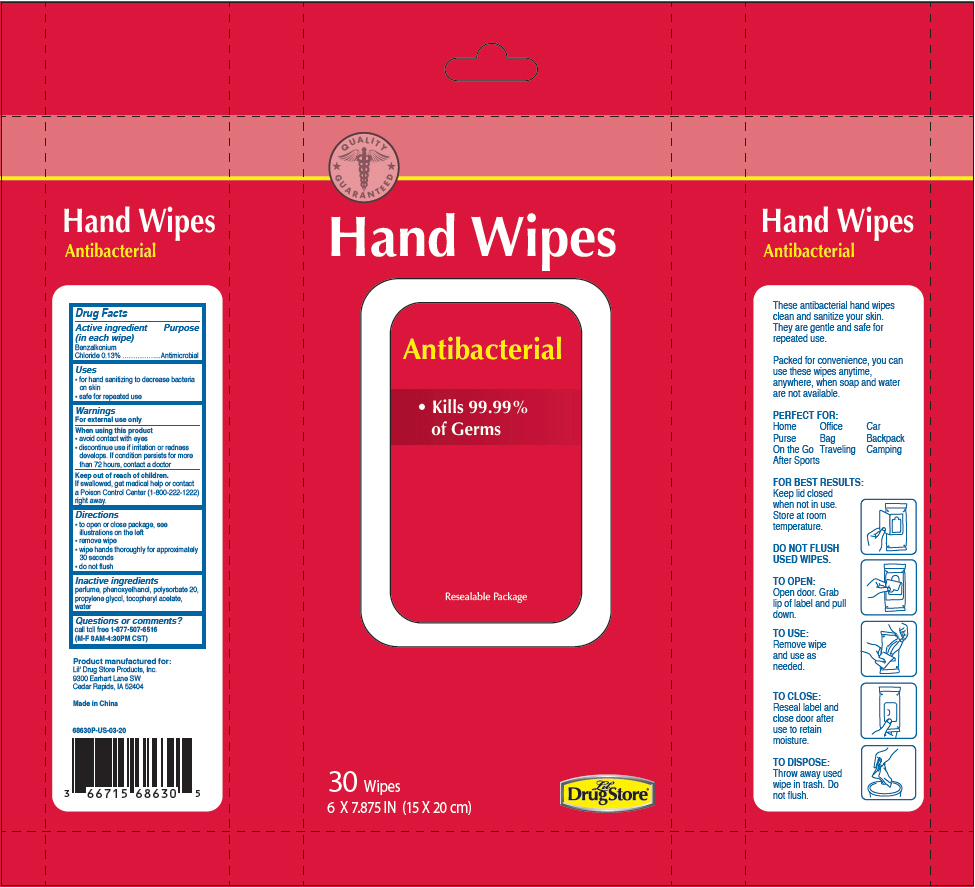 DRUG LABEL: Antibacterial Hand Wipes
NDC: 66715-6863 | Form: CLOTH
Manufacturer: Lil' Drug Store Products, Inc.
Category: otc | Type: HUMAN OTC DRUG LABEL
Date: 20241231

ACTIVE INGREDIENTS: BENZALKONIUM CHLORIDE 1.3 mg/1 mL
INACTIVE INGREDIENTS: PHENOXYETHANOL; POLYSORBATE 20; PROPYLENE GLYCOL; .ALPHA.-TOCOPHEROL ACETATE; WATER

Antibacterial Hand Wipes
Lil' Drug Store®

Drug Facts

Active ingredient (in each wipe)

Benzalkonium Chloride 0.13%

Purpose

Antimicrobial

Uses

- for hand sanitizing to decrease bacteria on skin
- safe for repeated use

Warnings

For external use only

When using this product

- avoid contact with eyes
- discontinue use if irritation or redness develops. If condition persists for more than 72 hours, contact a doctor

Keep out of reach of children.

If swallowed, get medical help or contact a Poison Control Center (1-800-222-1222) right away.

Directions

- to open or close package, see illustrations on the left
- remove wipe
- wipe hands thoroughly for approximately 30 seconds
- do not flush

Inactive ingredients

perfume, phenoxyethanol, polysorbate 20, propylene glycol, tocopheryl acetate, water

Questions or comments?

call toll free 1-877-507-6516
(M-F 8AM-4:30PM CST)

PRINCIPAL DISPLAY PANEL - 30 Wipe Bag

QUALITY
GUARANTEED

Hand Wipes

Antibacterial

- Kills 99.99%
  of Germs

Resealable Package

30 Wipes
6 X 7.875 IN (15 X 20 cm)

Lil'
Drug Store®